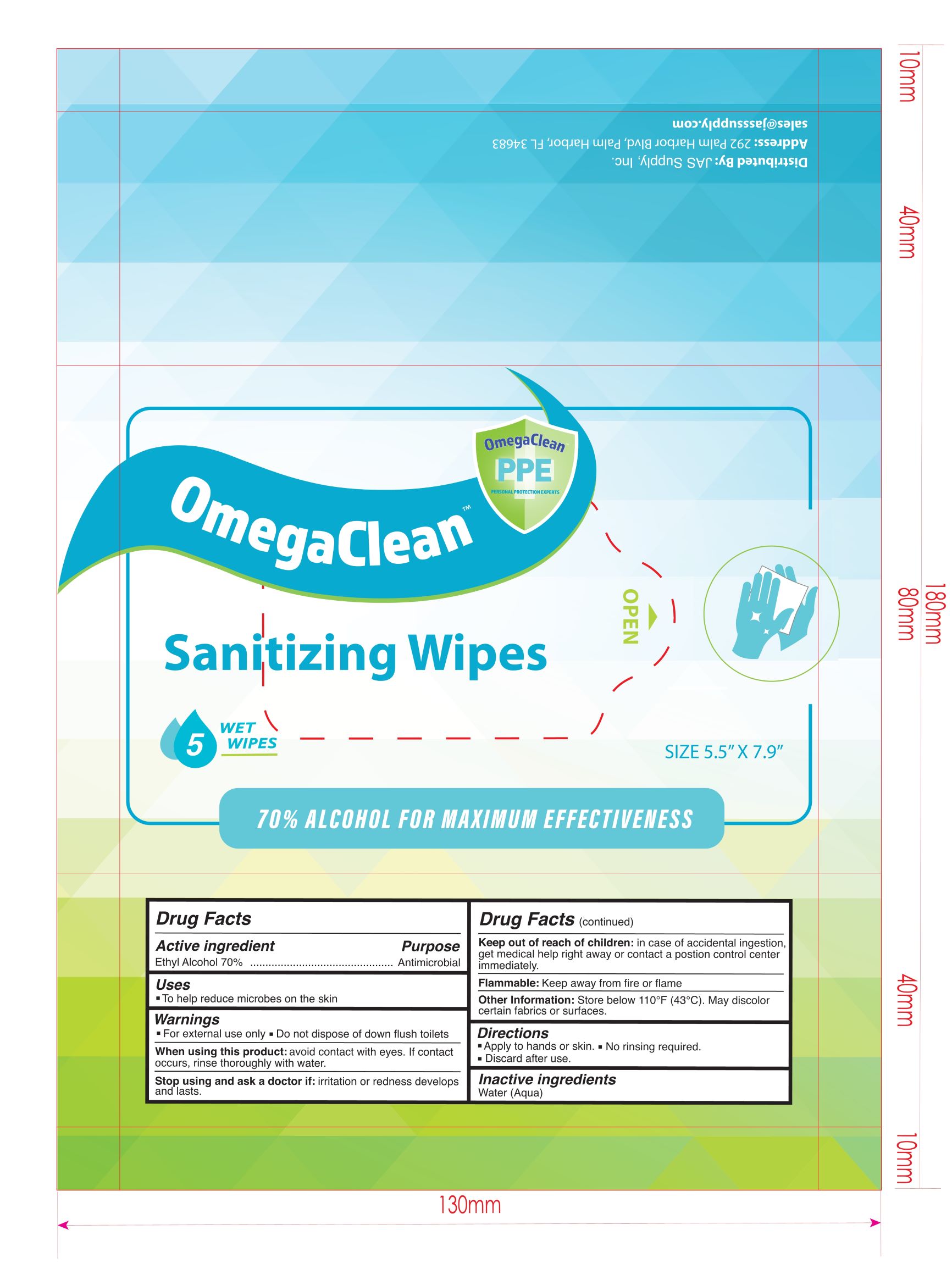 DRUG LABEL: Sanitizing Wipes
NDC: 79805-010 | Form: CLOTH
Manufacturer: JUXIN (Jiangsu) New Material Packaging Co., Ltd.
Category: otc | Type: HUMAN OTC DRUG LABEL
Date: 20221213

ACTIVE INGREDIENTS: ALCOHOL 70 mL/100 mL
INACTIVE INGREDIENTS: WATER

79805-010
Sanitizing Wipes 5pcs

Active Ingredient(s)

Ethyl Alcohol 70%

Purpose

Antimicrobial

Use

To help reduce microbes on the skin.

Warnings

- For external use only.
- Do not dispose of down flush toilets.
- Flammable: Keep away from fire or flame.

When using this product: avoid contact with eyes. lf contact occurs, rinse thoroughly with water.

STOP USE

Stop using and ask a doctor if: irritation or redness develops and lasts.

Keep out of reach of children: ln case of accidental ingestion, get medical help right away or contact a poison control center immediately.

Directions

- Apply to hands or skin.
- No rinsing required.
- Discard after use.

Other information

- Store below 110 °F（43° C).
- May discolor certain fabrics or surfaces.

Inactive ingredients

Water(Aqua).

Package Label - Principal Display Panel

5pcs NDC: 79805-010-01